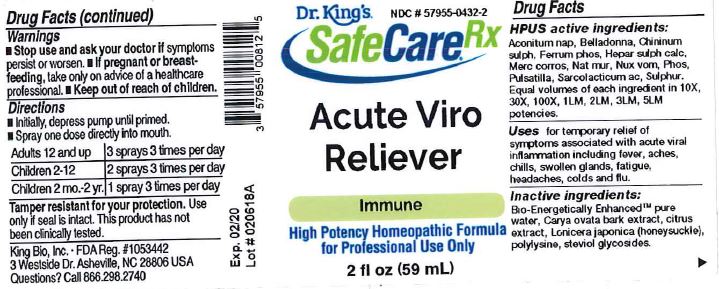 DRUG LABEL: Acute Viro Reliever
NDC: 57955-0432 | Form: LIQUID
Manufacturer: King Bio Inc.
Category: homeopathic | Type: HUMAN OTC DRUG LABEL
Date: 20180320

ACTIVE INGREDIENTS: ACONITUM NAPELLUS 10 [hp_X]/59 mL; ATROPA BELLADONNA 10 [hp_X]/59 mL; QUININE SULFATE 10 [hp_X]/59 mL; FERROSOFERRIC PHOSPHATE 10 [hp_X]/59 mL; CALCIUM SULFIDE 10 [hp_X]/59 mL; MERCURIC CHLORIDE 10 [hp_X]/59 mL; SODIUM CHLORIDE 10 [hp_X]/59 mL; STRYCHNOS NUX-VOMICA SEED 10 [hp_X]/59 mL; PHOSPHORUS 10 [hp_X]/59 mL; PULSATILLA VULGARIS 10 [hp_X]/59 mL; LACTIC ACID, L- 10 [hp_X]/59 mL; SULFUR 10 [hp_X]/59 mL
INACTIVE INGREDIENTS: WATER; CARYA OVATA BARK; CITRUS BIOFLAVONOIDS; LONICERA JAPONICA FLOWER; POLYEPSILON-LYSINE (4000 MW); REBAUDIOSIDE A

Acute Viro Reliever

HPUS active ingredients:

Aconitum nap, Belladonna, Chininum sulph, Ferrum phos, Hepar sulph calc, Merc corros, Nat mur, Nux vom, Phos, Pulsatilla, Sarcolacticum ac, Sulphur. Equal volumes of each ingredient in 10X, 30X, 100X, 1LM, 2LM, 3LM, 5LM potencies.

PURPOSE

Uses for temporary relief of symptoms associated with acute viral inflammation including fever, aches, chills, swollen glands, fatigue, headaches, colds and flu.

Inactive Ingredients:

Bio-Energetically Enhanced™ pure water base, Carya ovata bark extract, citrus extract, Lonicera japonica (honeysuckle), polylysine, steviol glycosides.

Warning

- Stop use and ask a doctor if symptoms persist or worsen.
- If pregnant or breast-feeding, take only on advice of a healthcare professional.

- Keep out of reach of children.

Directions

- Initially, depress pump until primed.
- Spray one dose directly into mouth.
- Adults 12 and up: 3 sprays 3 times per day.
- Children 2-12: 2 sprays 3 times per day.
- Children 2 mo.-2 yr: 1 spray 3 times per day

Other Information:

- Tamper resistant for your protection.
- Use only if seal is intact.
- This product has not been clinically tested.

INDICATIONS AND USAGE

Uses for temporary relief of symptoms associated with acute viral inflammation including:

- fever
- aches
- chills
- swollen glands
- fatigue
- headaches
- colds and flu